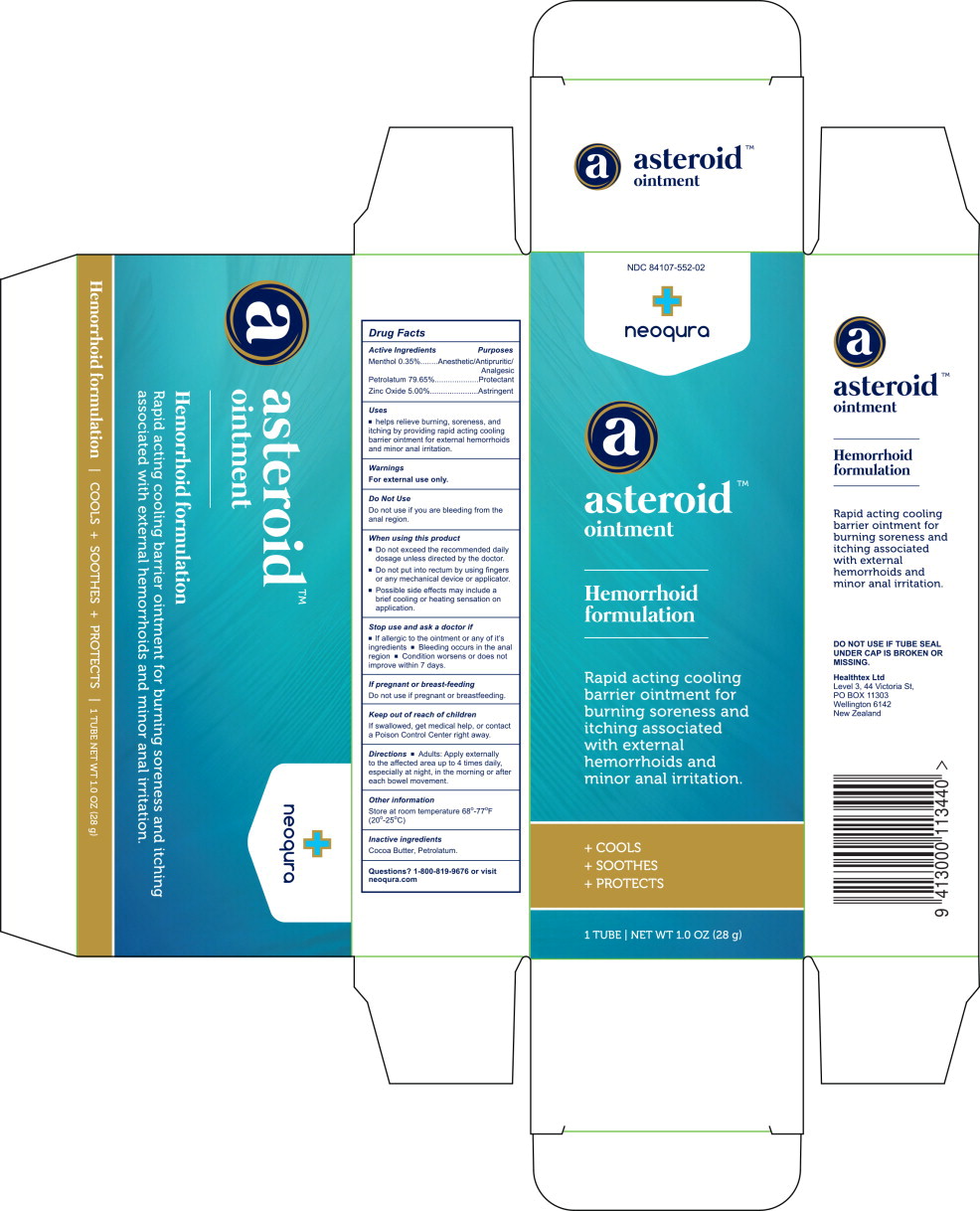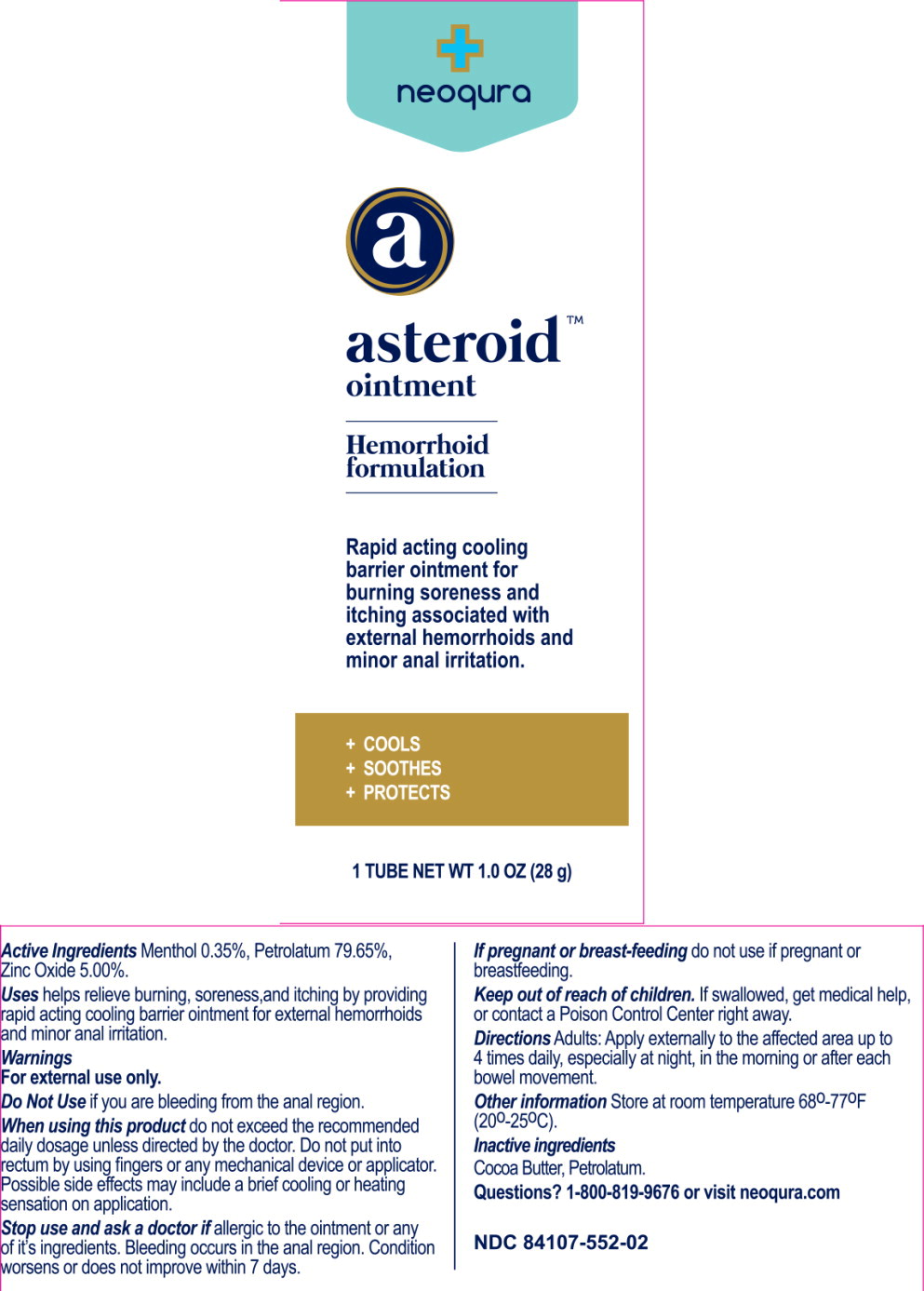 DRUG LABEL: Asteroid
NDC: 84107-552 | Form: OINTMENT
Manufacturer: HEALTHTEX LIMITED
Category: otc | Type: HUMAN OTC DRUG LABEL
Date: 20250730

ACTIVE INGREDIENTS: Menthol 0.098 g/28 g; Petrolatum 22.302 g/28 g; Zinc Oxide 1.4 g/28 g
INACTIVE INGREDIENTS: Cocoa Butter

Drug Facts

Active Ingredients

Menthol 0.35%

Petrolatum 79.65%

Zinc Oxide 5.00%

Purposes

Anesthetic/Antipruritic/Analgesic

Protectant

Astringent

Uses

- helps relieve burning, soreness, and itching by providing rapid acting cooling barrier ointment for external hemorrhoids and minor anal irritation.

Warnings

For external use only.

Do not use if you are bleeding from the anal region.

When using this product

- Do not exceed the recommended daily dosage unless directed by the doctor.
- Do not put into rectum by using fingers or any mechanical device or applicator.
- Possible side effects may include a brief cooling or heating sensation on application.

Stop use and ask a doctor if

- If allergic to the ointment or any of it's ingredients
- Bleeding occurs in the anal region
- Condition worsens or does not improve within 7 days.

If pregnant or breast-feeding

Do not use if pregnant or breastfeeding.

Keep out of reach of children

If swallowed, get medical help, or contact a Poison Control Center right away.

Directions

- Adults: Apply externally to the affected area up to 4 times daily, especially at night, in the morning or after each bowel movement.

Other information

Store at room temperature 68°-77°F (20°-25°C)

Inactive ingredients

Cocoa Butter, Petrolatum.

Questions?

1-800-819-9676 or visit neoqura.com

Principal Display Panel – 28 g Carton Label

NDC 84107-552-02

neoqura

asteroid™
ointment

Hemorrhoid
formulation

Rapid acting cooling
barrier ointment for
burning soreness and
itching associated
with external
hemorrhoids and
minor anal irritation.

+ COOLS

+ SOOTHES

+ PROTECTS

1 TUBE | NET WT 1.0 OZ (28 g)

Principal Display Panel – 28 g Tube Label

neoqura

asteroid™
ointment

Hemorrhoid
formulation

Rapid acting cooling
barrier ointment for
burning soreness and
itching associated with
external hemorrhoids and
minor anal irritation.

+ COOLS

+ SOOTHES

+ PROTECTS

1 TUBE NET WT 1.0 OZ (28 g)